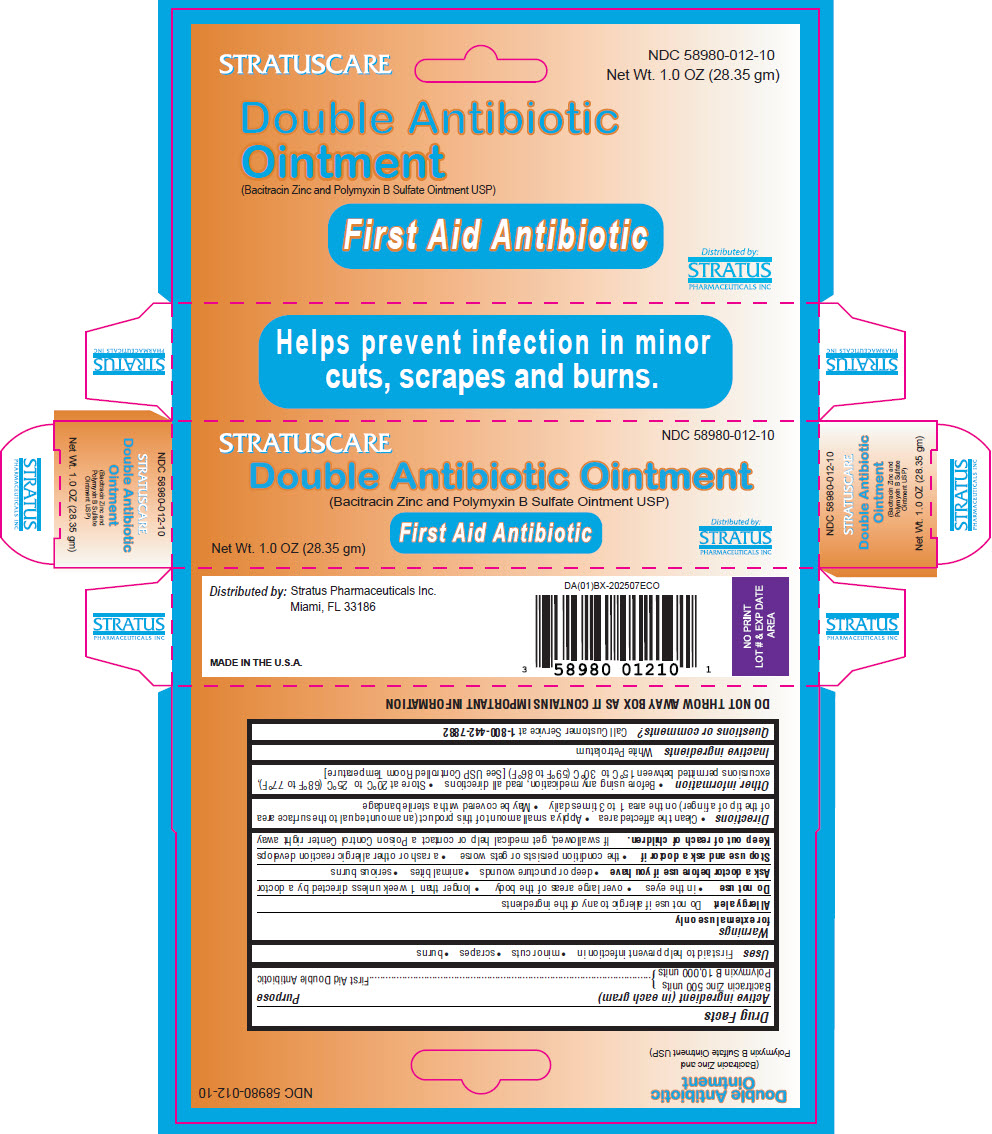 DRUG LABEL: Double Antibiotic
NDC: 58980-012 | Form: OINTMENT
Manufacturer: STRATUS PHARMACEUTICALS INC
Category: otc | Type: HUMAN OTC DRUG LABEL
Date: 20260204

ACTIVE INGREDIENTS: BACITRACIN ZINC 500 [USP'U]/1 g; POLYMYXIN B SULFATE 10000 [USP'U]/1 g
INACTIVE INGREDIENTS: PETROLATUM

Double Antibiotic Ointment

Drug Facts

ACTIVE INGREDIENT

Active ingredient (in each gram) | Purpose
Bacitracin Zinc 500 units | First Aid Double Antibiotic
Polymyxin B 10,000 units | First Aid Double Antibiotic

Uses

First aid to help prevent infection in

- minor cuts
- scrapes
- burns

Warnings

for external use only

Allergy alert

Do not use if allergic to any of the ingredients

Do not use

- in the eyes
- over large areas of the body
- longer than 1 week unless directed by a doctor

Ask a doctor before use if you have

- deep or puncture wounds
- animal bites
- serious burns

Stop use and ask a doctor if

- the condition persists or gets worse
- a rash or other allergic reaction develops

Keep out of reach of children. If swallowed, get medical help or contact a Poison Control Center right away

Directions

- Clean the affected area
- Apply a small amount of this product (an amount equal to the surface area of the tip of a finger) on the area 1 to 3 times daily
- May be covered with a sterile bandage

Other information

- Before using any medication, read all directions
- Store at 20°C to 25°C (68°F to 77°F), excursions permitted between 15°C to 30°C (59°F to 86°F) [See USP Controlled Room Temperature]

Inactive ingredients

White Petrolatum

Questions or comments?

Call Customer Service at 1-800-442-7882

Distributed by: Stratus Pharmaceuticals Inc.
Miami, FL 33186

PRINCIPAL DISPLAY PANEL - 28.35 gm Tube Box

NDC 58980-012-10

STRATUSCARE
Double Antibiotic Ointment
(Bacitracin Zinc and Polymyxin B Sulfate Ointment USP)

First Aid Antibiotic

Net Wt. 1.0 OZ (28.35 gm)

Distributed by:
STRATUS
PHARMACEUTICALS INC